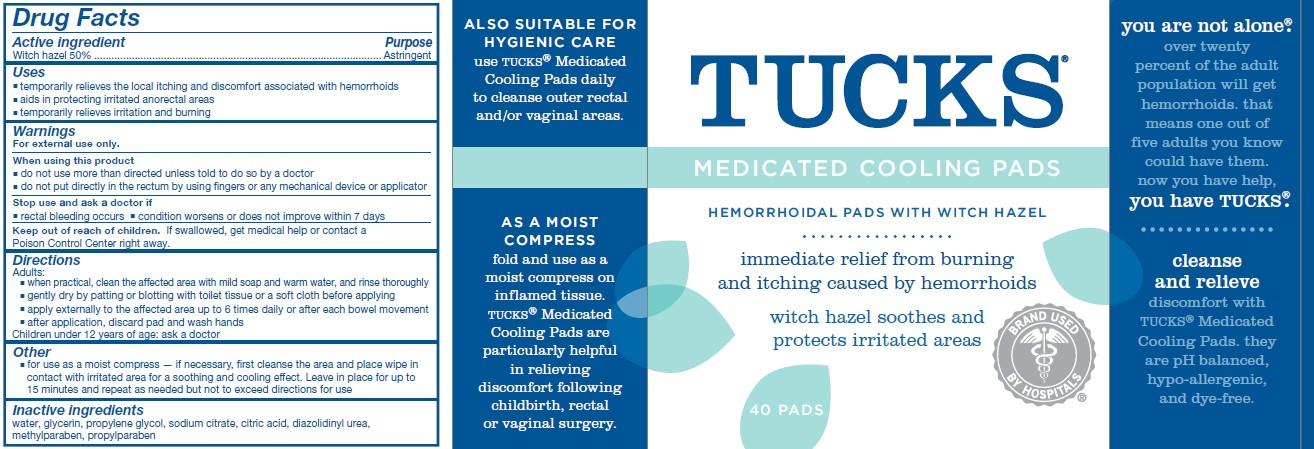 DRUG LABEL: Tucks
NDC: 44038-0213 | Form: SOLUTION
Manufacturer: Accupac LLC
Category: otc | Type: HUMAN OTC DRUG LABEL
Date: 20240918

ACTIVE INGREDIENTS: WITCH HAZEL 500 mg/1 mL
INACTIVE INGREDIENTS: GLYCERIN; ETHYLHEXYLGLYCERIN; WATER; SODIUM CITRATE, UNSPECIFIED FORM; CITRIC ACID MONOHYDRATE; PHENOXYETHANOL; EDETATE DISODIUM; POTASSIUM SORBATE

Active ingredient

Witch hazel (50% w/w)

Purpose

Astringent

Uses

temporarily relieves the local itching and discomfort associated with hemorrhoids

aids in protecting irritated ahorectal areas

temporarily relieves irritation and burning

Warnings

Stop use and ask a doctor if

rectal bleeding occurs

condition worsens or does not improve within 7 days

Keep out of the reach of children.

If swallowed, get medical help or call a Poison Control Center right away.

Directions

Adults:

when practical, clean the affected area with mild soap and warm water, and rinse thoroughly

gently dry by patting or blotting with toilet tissue or a soft cloth before applying

apply externally fot the affected area up to 6 times daily or after each bowel movement

Children under 12 years of age: ask a doctor

Other information

DO NOT FLUSH-after application, discard pad in trash and wash hands

for use as a moist compress--if necessary, first cleanse the area and place the wipe in contact with the irritated area for a soothing and cooling effect. Leave in place for up to 15 minutes and repeat as needed but not to exceed directions for use

Inactive ingredients

Water

Glycerin

Sodium Citrate, Unspecified form

Citric Acid Monohydrate

Ethylhexylglycerin

Phenoxyethanol

Edetate Disodium

Potassium Sorbate